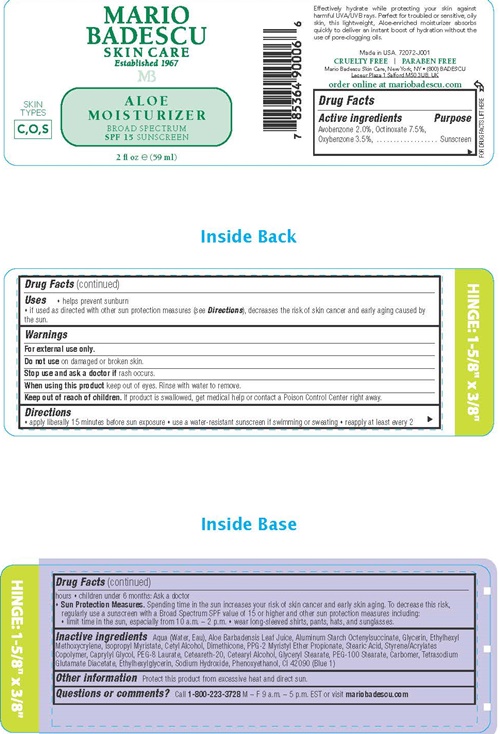 DRUG LABEL: MARIO BADESCU ALOE SPF
NDC: 54111-137 | Form: LOTION
Manufacturer: Bentley Laboratories LLC
Category: otc | Type: HUMAN OTC DRUG LABEL
Date: 20240910

ACTIVE INGREDIENTS: AVOBENZONE 1.2 g/59 mL; OCTINOXATE 4.24 g/59 mL; OXYBENZONE 2.0 g/59 mL
INACTIVE INGREDIENTS: WATER; ALOE VERA LEAF; ALUMINUM STARCH OCTENYLSUCCINATE; GLYCERIN; ETHYLHEXYL METHOXYCRYLENE; ISOPROPYL MYRISTATE; CETYL ALCOHOL; DIMETHICONE; PPG-2 MYRISTYL ETHER PROPIONATE; STEARIC ACID; STYRENE/ACRYLAMIDE COPOLYMER (MW 500000); CAPRYLYL GLYCOL; PEG-8 LAURATE; POLYOXYL 20 CETOSTEARYL ETHER; CETOSTEARYL ALCOHOL; GLYCERYL MONOSTEARATE; PEG-100 STEARATE; CARBOXYPOLYMETHYLENE; TETRASODIUM GLUTAMATE DIACETATE; ETHYLHEXYLGLYCERIN; SODIUM HYDROXIDE; PHENOXYETHANOL; FD&C BLUE NO. 1

MARIO BADESCU Aloe Moisturizer SPF 15

Drug Facts Active ingredients

Avobenzone 2.0%
Octinoxate 7.5%
Oxybenzone 3.5%

Purpose

Sunscreen

Uses

- helps prevent sunburn
- If used as directed with other sun protection measures (see Directions), decreases the risk of skin cancer and early aging caused by the sun.

Warnings

For external use only.

Do not use on damaged or broken skin.

Stop use and ask a doctor if rash occurs.

When using this product keep out of eyes. Rinse with water to remove

Keep out of reach of children.

If product is swallowed, get medical help or contact a Poison Control Center right away.

Directions

- apply liberally 15 minutes before sun exposure
- use a water-resistant sunscreen if swimming or sweating
- reapply at least every 2 hours
- children under 6 months: Ask a doctor
- Sun Protection Measures. Spending time in the sun increases your risk of skin cancer and early aging. To decrease this risk, regularly use a sunscreen with a Broad Spectrum SPF value of 15 or higher and other sun protectionmeasures including:
- limit time in the sun, especially from 10 a.m. - 2 p.m.
- wear long-sleeved shirts, pants, hats, and sunglasses.

Inactive ingredients

Aqua (Water, Eau), Aloe Barbadensis Leaf Juice, Aluminum Starch Octenylsuccinate, Glycerin, Ethylhexyl Methoxycrylene, Isopropyl Myristate, Cetyl Alcohol, Dimethicone, PPG-2 Myristyl Ether Propionate, Stearic Acid, Styrene/Acrylates Copolymer, Caprylyl Glycol, PEG-8 Laurate, Ceteareth-20, Cetearyl Alcohol, Glyceryl Stearate, PEG-100 Stearate, Carbomer, Tetrasodium Glutamate Diacetate, Ethylhexlglycerin, Sodium Hydroxide, Phenoxyethanol, Cl 42090 (Blue 1)

Other information

Protect this product from excessive heat and direct sun,

Questions or comments?

Call 1-800-223-3728 M - F 9 a.m. - 5 p.m. EST or visit mariobadescu.com

MARIO BADESCU SKIN CARE Aloe Moisturizer SPF 15 SUNSCREEN product label

MARIO
BADESCU
SKIN CARE
Established 1967
MB
Aloe
Moisturizer
BROAD SPECTRUM
SPF15 SUNSCREEN

2 fl oz (59 ml)

Effectively hydrate while protecting your skin against harmful UVA/UVB rays. Perfect for troubled or sensitive, oily skin, this light weight, Aloe-enriched moisturizer absorbs quickly to deliver an instant boost of hydration without the pore-clogging oils.

Made in the USA. 72072-J001
CRUELTY FREE l PARABEN FREE
Mario Badescu Skin Care, New York, NY • (800) BADESCU
Leceur Plaza 1 Salford M50 3UB, UK

order online at mario bedescu.com

res